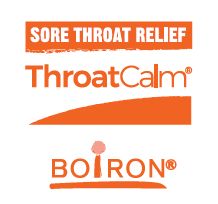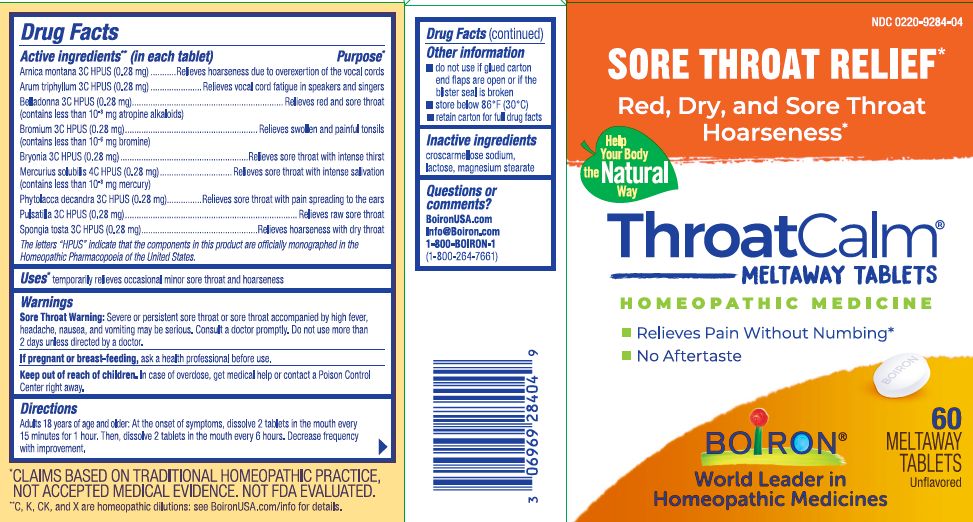 DRUG LABEL: ThroatCalm
NDC: 0220-9284 | Form: TABLET
Manufacturer: Boiron
Category: homeopathic | Type: HUMAN OTC DRUG LABEL
Date: 20260215

ACTIVE INGREDIENTS: SPONGIA OFFICINALIS SKELETON, ROASTED 3 [hp_C]/1 1; BROMINE 3 [hp_C]/1 1; MERCURIUS SOLUBILIS 4 [hp_C]/1 1; PULSATILLA VULGARIS 3 [hp_C]/1 1; ARNICA MONTANA 3 [hp_C]/1 1; PHYTOLACCA AMERICANA ROOT 3 [hp_C]/1 1; ARISAEMA TRIPHYLLUM ROOT 3 [hp_C]/1 1; ATROPA BELLADONNA 3 [hp_C]/1 1; BRYONIA ALBA ROOT 3 [hp_C]/1 1
INACTIVE INGREDIENTS: CROSCARMELLOSE SODIUM; LACTOSE; MAGNESIUM STEARATE

ThroatCalm 18+ Tablets

Active ingredients** (in each tablet)

Arnica montana 3C HPUS (0.28 mg)

Arum triphyllum 3C HPUS (0.28 mg)

Belladonna 3C HPUS (0.28 mg) (contains less than 10^-8 mg atropine alkaloids)

Bromium 3C HPUS (0.28 mg) (contains less than 10^-6 mg bromine)

Bryonia 3C HPUS (0.28 mg)

Mercurius solubilis 4C HPUS (0.28 mg) (contains less than 10^-8 mg mercury)

Phytolacca decandra 3C HPUS (0.28 mg)

Pulsatilla 3C HPUS (0.28 mg)

Spongia tosta 3C HPUS (0.28 mg)

The letters "HPUS" indicate that the components in this product are officially monographed in the Homeopathic Pharmacopoeia of the United States.

Purpose*

Arnica montana 3C HPUS (0.28 mg)……..……Relieves hoarseness due to overexertion of the vocal cords

Arum triphyllum 3C HPUS (0.28 mg).…………….………..Relieves vocal cord fatigue in speakers and singers

Belladonna 3C HPUS (0.28 mg) ……………………....………………………………………..Relieves red and sore throat

Bromium 3C HPUS (0.28 mg)…………….………………………………………..…Relieves swollen and painful tonsils

Bryonia 3C HPUS (0.28 mg)….…………..…………………………………..…Relieves sore throat with intense thirst

Mercurius solubilis 4C HPUS (0.28 mg)…………………………..…Relieves sore throat with intense salivation

Phytolacca decandra 3C HPUS (0.28 mg)………….…Relieves sore throat with pain spreading to the ears

Pulsatilla 3C HPUS (0.28 mg)………………...………………..………………….……..………....Relieves raw sore throat

Spongia tosta 3C HPUS (0.28 mg)……………………..…….…………………..Relieves hoarseness with dry throat

Uses*

temporarily relieves occasional minor sore throat and hoarseness

WARNINGS

Sore Throat Warning: Severe or persistent sore throat or sore throat accompanied by high fever, headache, nausea, and vomiting may be serious. Consult a doctor promptly. Do not use more than 2 days unless directed by a doctor.

PREGNANCY OR BREAST FEEDING

If pregnant or breast-feeding, ask a health professional before use.

Keep out of reach of children. In case of overdose, get medical help or contact a Poison Control Center right away.

DOSAGE AND ADMINISTRATION

Adults 18 years of age and older: At the onset of symptoms, dissolve 2 tablets in the mouth every 15 minutes for 1 hour. Then, dissolve 2 tablets in the mouth every 6 hours. Decrease frequency with improvement.

Other information

- do not use if glued carton end flaps are open or if the blister seal is broken
- store below 86°F (30°C)
- retain carton for full drug facts

INACTIVE INGREDIENT

croscarmellose sodium, lactose, magnesium stearate

QUESTIONS

BoironUSA.com

Info@Boiron.com

1-800-BOIRON-1 (1-800-264-7661)

Made in France

Distributed by Boiron Inc.

Newtown Square, PA 19073

SORE THROAT RELIEF*

Red, Dry, and Sore Throat

Hoarseness*

- Relieves Pain Without Numbing*
- No Aftertaste

60 Meltaway Tablets

*CLAIMS BASED ON TRADITIONAL HOMEOPATHIC PRACTICE, NOT ACCEPTED MEDICAL EVIDENCE. NOT FDA EVALUATED.
**C, K, CK, and X are homeopathic dilutions: see BoironUSA.com/info for details.